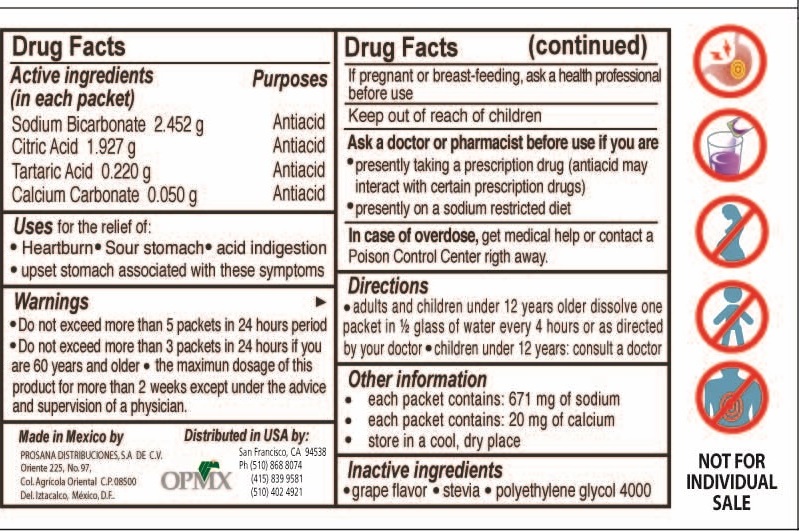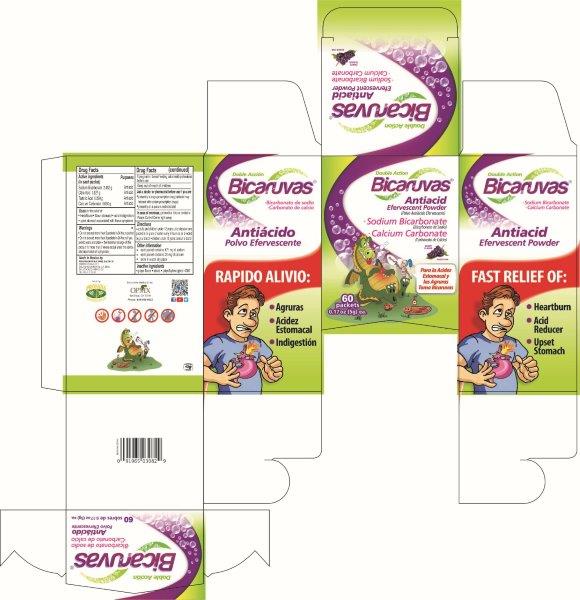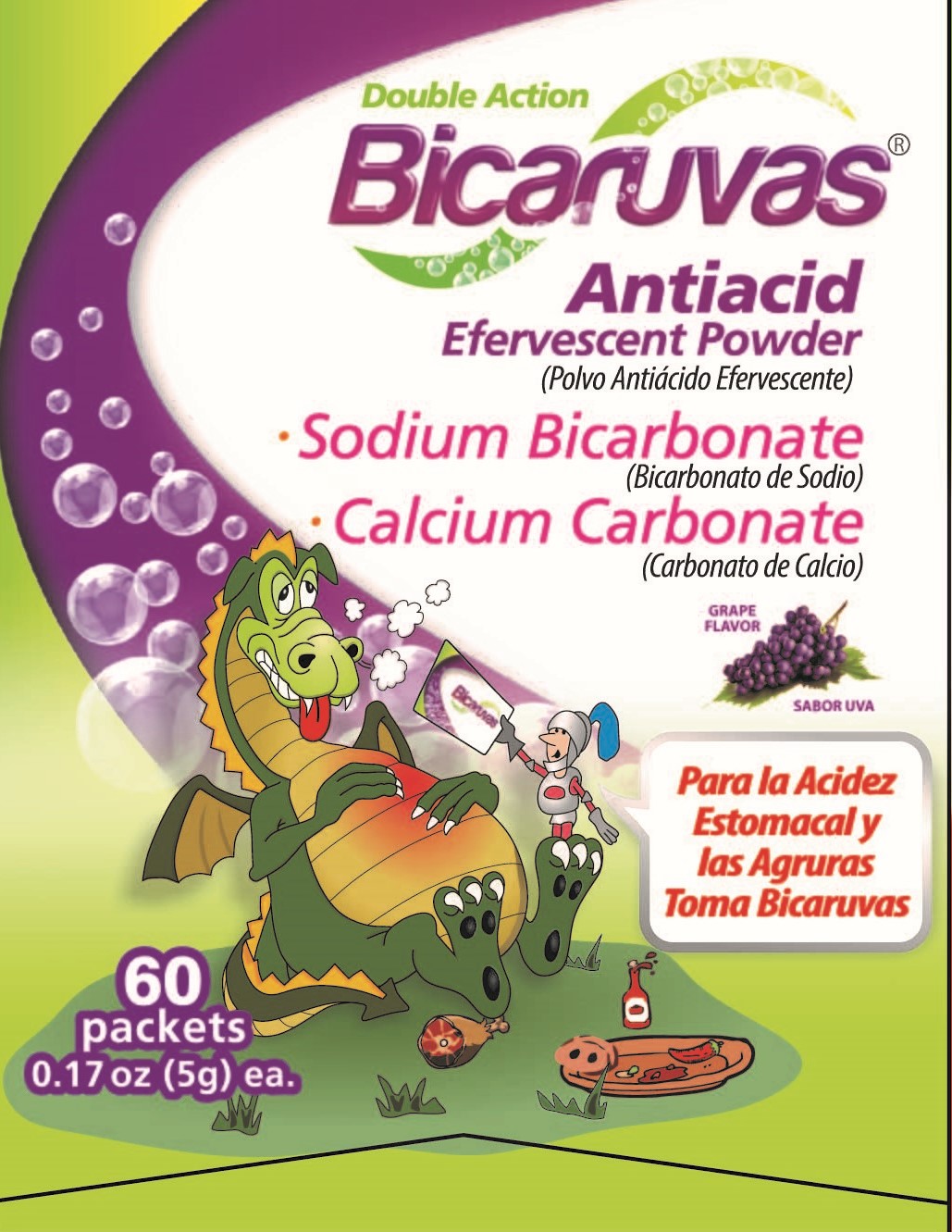 DRUG LABEL: BICARUVAS
NDC: 69728-0003 | Form: POWDER, FOR SOLUTION
Manufacturer: PROSANA DISTRIBUCIONES, S.A. DE C.V.
Category: otc | Type: HUMAN OTC DRUG LABEL
Date: 20160613

ACTIVE INGREDIENTS: TARTARIC ACID 2 g/944 mL; CALCIUM CARBONATE 1 g/944 mL; CITRIC ACID MONOHYDRATE 15 g/944 mL; SODIUM BICARBONATE 19 g/944 mL
INACTIVE INGREDIENTS: GRAPE 1 g/944 mL; STEVIA LEAF 1 g/944 mL; POLYETHYLENE GLYCOL 4000 1 g/944 mL

Bicaruvas Double Action Antacid 60 pack

Active ingredients

Active Ingredients (in each packet) Purpose

Sodium Bicarbonate 2.452g antacid

Citric Acid 1.927 g antiacid

Tartaric Acid 0.220g antiacid

Calcium Carbonate .05 g antiacid

Uses

Uses for the relief of:

Heartburn . Sour stomach . upset stomach associated with these symptoms

Warnings

Warnings Do not exceed more than 5 packets in a 24 hour period

Do not exceed more than 3 packets in 24 hours if you are 60 years or older

the maximum dosage for more than two weeks except under the advise and supervision of a physician

Pregnant

If pregnant or breat feeding, ask a helth professional before use

Overdose

In case of Overdose get medical help or contact a Poison Control Center right away.

Inactive

Inactive Ingredients

grape flavor. stevia. polyethilene glycol 4000

Other Information

each packet contains 671 mg of sodium

each packet contains 20 mg of calcium

store in a dry cool place

children

Keep out of reach of children

Bicaruvas Statement of identity Please see front60.jpg

Double Action

BICARUVAS

.Sodium Bicarbonate

.Calcium Carbonate

Antiacid

Effervescent Powder

60 packets .17 oz (5g) ea.

Directions

.Adult and children 12 years older dissolve one packet in 1/2 glass of water every 4 hours or as directed by your doctor.

Children under 12 years, consult a doctor

Principal Display Please see box.jpg

BICARUVAS

DOUBLE ACTION

Bicaruvas

Sodium Bicarbonate

Calcium Carbonate

Antacid

Effervescent powder

60 packets 0.17 oz (5g) ea